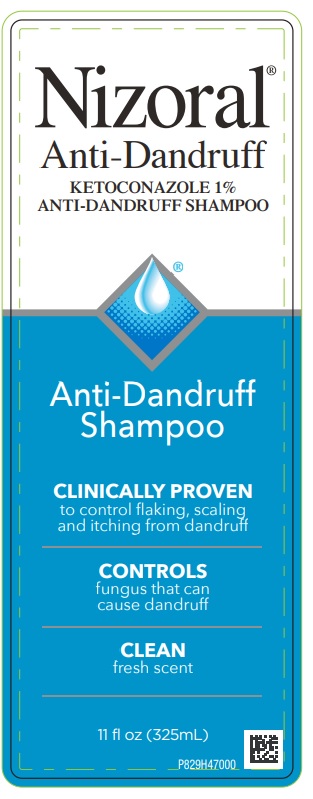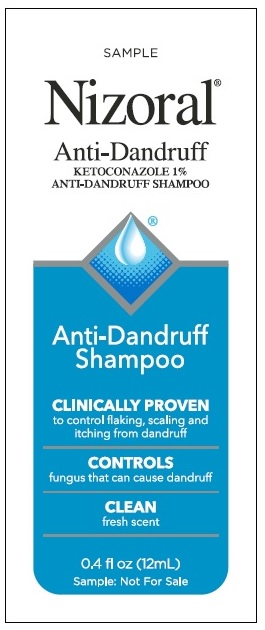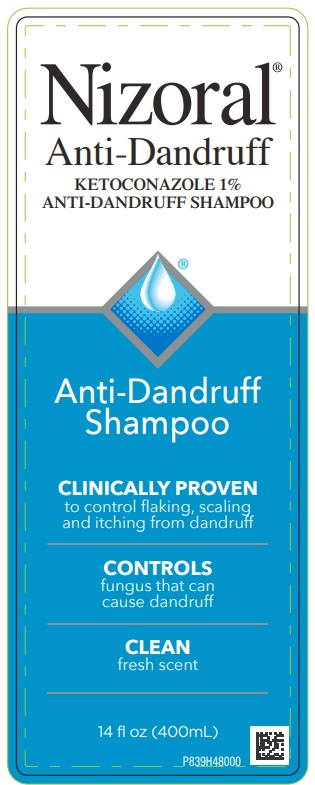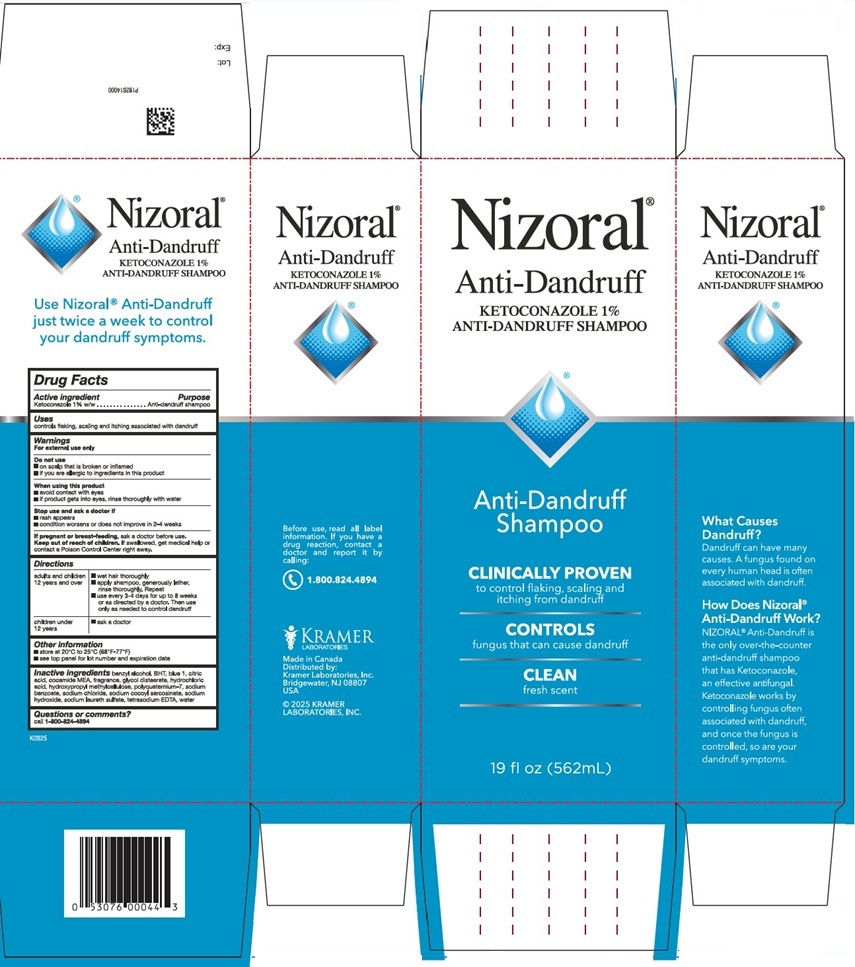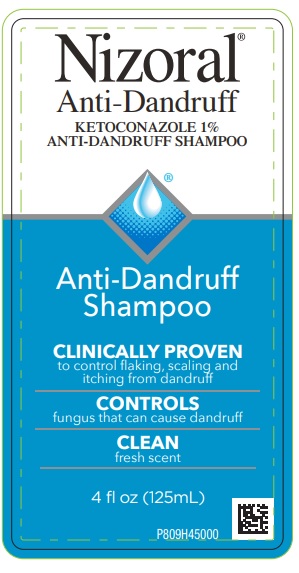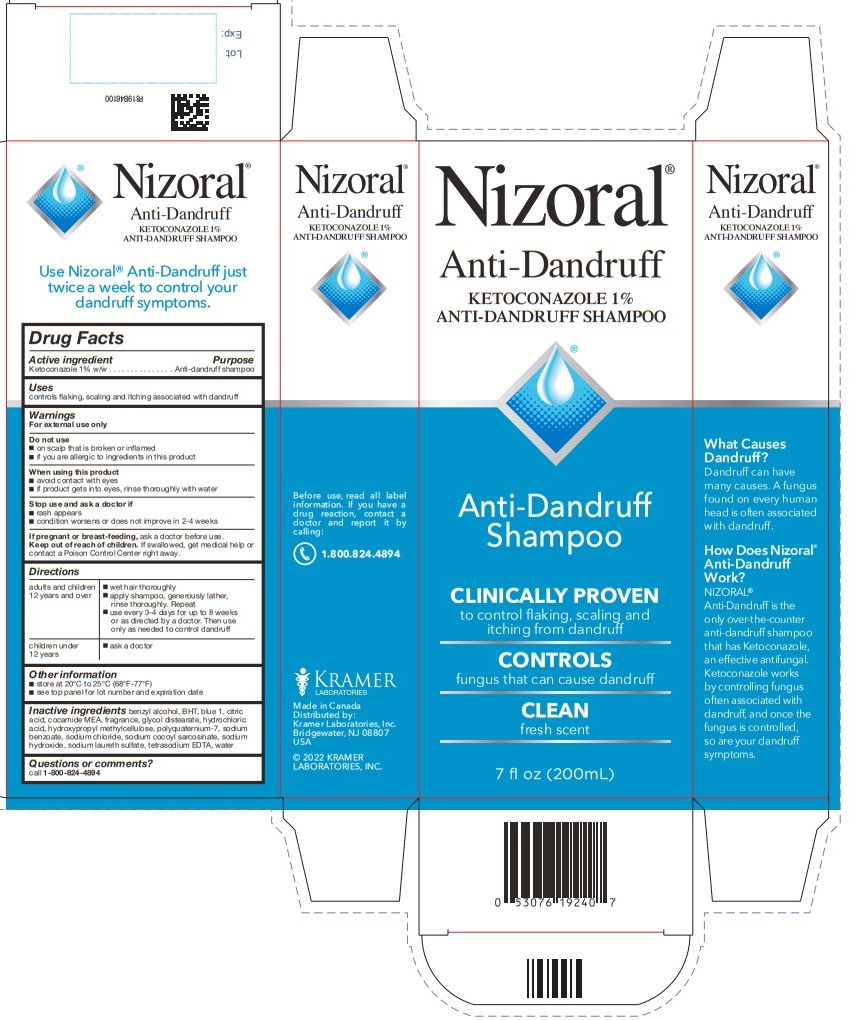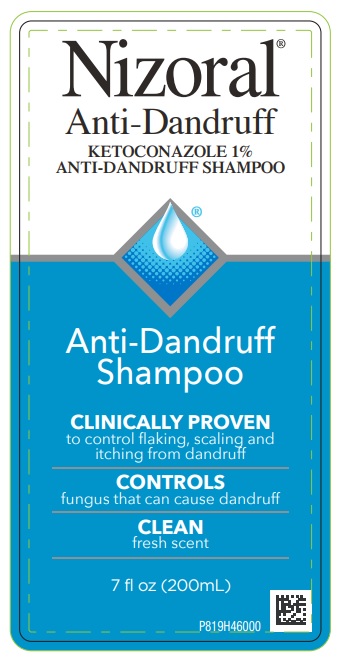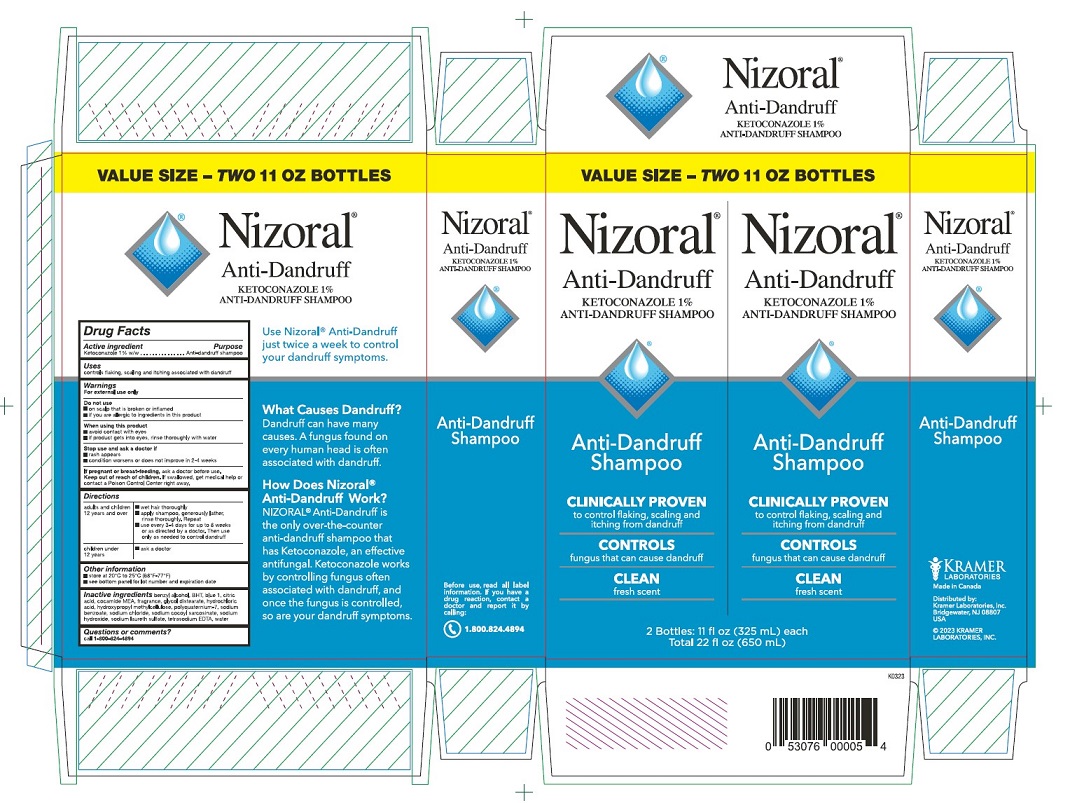 DRUG LABEL: Nizoral
NDC: 55505-196 | Form: SHAMPOO
Manufacturer: Kramer Laboratories
Category: otc | Type: HUMAN OTC DRUG LABEL
Date: 20251223

ACTIVE INGREDIENTS: Ketoconazole 10 mg/1 mL
INACTIVE INGREDIENTS: Benzyl Alcohol; Butylated Hydroxytoluene; Fd&C Blue No. 1; Citric Acid Monohydrate; Coco Monoethanolamide; Glycol Distearate; Hydrochloric Acid; Hypromellose, Unspecified; Polyquaternium-7 (70/30 Acrylamide/Dadmac; 1600000 Mw); Sodium Chloride; Sodium Cocoyl Sarcosinate; Sodium Hydroxide; Sodium Laureth-3 Sulfate; Edetate Sodium; Water

Drug Facts

ACTIVE INGREDIENT

Active ingredient | Purpose
Ketoconazole 1% w/w | Anti-dandruff shampoo

Uses
controls flaking, scaling and itching associated with dandruff

Warnings
For external use only

Do not use

- on scalp that is broken or inflamed
- if you are allergic to ingredients in this product

When using this product

- avoid contact with eyes
- if product gets into eyes, rinse thoroughly with water

Stop use and ask a doctor if

- rash appears
- condition worsens or does not improve in 2-4 weeks

PREGNANCY OR BREAST FEEDING

If pregnant or breast-feeding, ask a doctor before use.

KEEP OUT OF REACH OF CHILDREN

Keep out of the reach of children. If swallowed, get medical help or
contact a Poison Control Center right away.

Directions

adults and children 12 years and over | - wet hair thoroughly - apply shampoo, generously lather, rinse thoroughly. Repeat - use every 3-4 days for up to 8 weeks or as directed by a doctor. Then use only as needed to control dandruff
children under 12 years | - ask a doctor

Other information

- store at 20°C to 25°C (68°F-77°F)
- see top panel for lot number and expiration date

Inactive ingredients

benzyl alcohol, BHT, blue 1, citric
acid, cocamide MEA, fragrance, glycol distearate, hydrochloric
acid, hydroxypropyl methylcellulose, polyquaternium-7, sodium
benzoate, sodium chloride, sodium cocoyl sarcosinate, sodium
hydroxide, sodium laureth sulfate, tetrasodium EDTA, water

Questions or comments?

call 1-800-824-4894

PRINCIPAL DISPLAY PANEL

Nizoral®
Anti-Dandruff
KETOCONAZOLE 1%
ANTI-DANDRUFF SHAMPOO
Anti-Dandruff
Shampoo
CLINICALLY PROVEN
to control flaking, scaling and
itching from dandruff
CONTROLS
fungus that can cause dandruff
CLEAN
fresh scent
7 fl oz (200mL)
What Causes
Dandruff?
Dandruff can have
many causes. A fungus
found on every human
head is often associated
with dandruff.
How Does Nizoral®
Anti-Dandruff
Work?
NIZORAL®
Anti-Dandruff is the
only over-the-counter
anti-dandruff shampoo
that has Ketoconazole,
an effective antifungal.
Ketoconazole works
by controlling fungus
often associated with
dandruff, and once the
fungus is controlled,
so are your dandruff
symptoms.
Use Nizoral® Anti-Dandruff just
twice a week to control your
dandruff symptoms.
Before use, read all label
information. If you have a
drug reaction, contact a
doctor and report it by calling:
1.800.824.4894
KRAMER
LABORATORIES
Made in Canada
Distributed by:
Kramer Laboratories, Inc.
Bridgewater, NJ 08807
USA
© 2022 KRAMER
LABORATORIES, INC.
Lot:
Exp:
P819B46100

Nizoral®
Anti-Dandruff
KETOCONAZOLE 1%
ANTI-DANDRUFF SHAMPOO
CONTROLS
fungus that can cause dandruff

Nizoral®
Anti-Dandruff
KETOCONAZOLE 1%
ANTI-DANDRUFF SHAMPOO
Anti-Dandruff
Shampoo
CLINICALLY PROVEN
to control flaking, scaling and
itching from dandruff
CONTROLS
fungus that can cause dandruff
CLEAN
fresh scent
7 fl oz (200mL)
P819H46000

Nizoral®
Anti-Dandruff
KETOCONAZOLE 1%
ANTI-DANDRUFF SHAMPOO
Anti-Dandruff
Shampoo
CLINICALLY PROVEN
to control flaking, scaling and
itching from dandruff
CONTROLS
fungus that can cause dandruff
CLEAN
fresh scent
4 fl oz (125mL)
P809H45000

Nizoral®
Anti-Dandruff
KETOCONAZOLE 1%
ANTI-DANDRUFF SHAMPOO
Anti-Dandruff
Shampoo
CLINICALLY PROVEN
to control flaking, scaling and
itching from dandruff
CONTROLS
fungus that can cause dandruff
CLEAN
fresh scent
11 fl oz (325mL)
P829H47000

Nizoral®
Anti-Dandruff
KETOCONAZOLE 1%
ANTI-DANDRUFF SHAMPOO
Anti-Dandruff
Shampoo
CLINICALLY PROVEN
to control flaking, scaling and
itching from dandruff
CONTROLS
fungus that can cause dandruff
CLEAN
fresh scent
14 fl oz (400 mL)
P839H48000

SAMPLE
Nizoral®
Anti-Dandruff
KETOCONAZOLE 1%
ANTI-DANDRUFF SHAMPOO
Anti-Dandruff
Shampoo
CLINICALLY PROVEN
to control flaking, scaling and
itching from dandruff
CONTROLS
fungus that can cause dandruff
CLEAN
fresh scent
0.4 fl oz (12 mL)
Sample Not For Sale

Nizoral®
Anti-Dandruff
KETOCONAZOLE 1%
ANTI-DANDRUFF SHAMPOO
VALUE SIZE - TWO 11 OZ BOTTLES
Anti-Dandruff
Shampoo
CLINICALLY PROVEN
to control flaking, scaling and
itching from dandruff
CONTROLS
fungus that can cause dandruff
CLEAN
fresh scent
2 Bottles: 11 fl oz (325 mL) each
Total 22 fl oz (650 mL)
Use Nizoral® Anti-Dandruff
just twice a week to control
your dandruff symptoms.
What Causes Dandruff?
Dandruff can have many
causes. A fungus found on
every human head is often
associated with dandruff.
How Does Nizoral®
Anti-Dandruff Work?
NIZORAL® Anti-Dandruff is
the only over-the-counter
anti-dandruff shampoo that
has Ketoconazole, an effective
antifungal. Ketoconazole works
by controlling fungus often
associated with dandruff, and
once the fungus is controlled,
so are your dandruff symptoms.
Anti-Dandruff
Shampoo
Before use, read all label
information. If you have a
drug reaction, contact a
doctor and report it by calling:
1.800.824.4894
KRAMER
LABORATORIES
Made in Canada
Distributed by:
Kramer Laboratories, Inc.
Bridgewater, NJ 08807
USA
© 2023 KRAMER
LABORATORIES, INC.

Nizoral®
Anti-Dandruff
KETOCONAZOLE 1%
ANTI-DANDRUFF SHAMPOO
Anti-Dandruff
Shampoo
CLINICALLY PROVEN
to control flaking, scaling and
itching from dandruff
CONTROLS
fungus that can cause dandruff
CLEAN
fresh scent
19 fl oz (562mL)
What Causes Dandruff?
Dandruff can have many
causes. A fungus found on
every human head is often
associated with dandruff.
How Does Nizoral®
Anti-Dandruff Work?
NIZORAL® Anti-Dandruff is
the only over-the-counter
anti-dandruff shampoo
that has Ketoconazole,
an effective antifungal.
Ketoconazole works by
controlling fungus often
associated with dandruff,
and once the fungus is
controlled, so are your
dandruff symptoms.
Use Nizoral® Anti-Dandruff
just twice a week to control
your dandruff symptoms.
Before use, read all label
information. If you have a
drug reaction, contact a
doctor and report it by
calling:
1.800.824.4894
KRAMER
LABORATORIES
Made in Canada
Distributed by:
Kramer Laboratories, Inc.
Bridgewater, NJ 08807
USA
© 2025 KRAMER
LABORATORIES, INC.
P192B14000
Lot:
Exp: